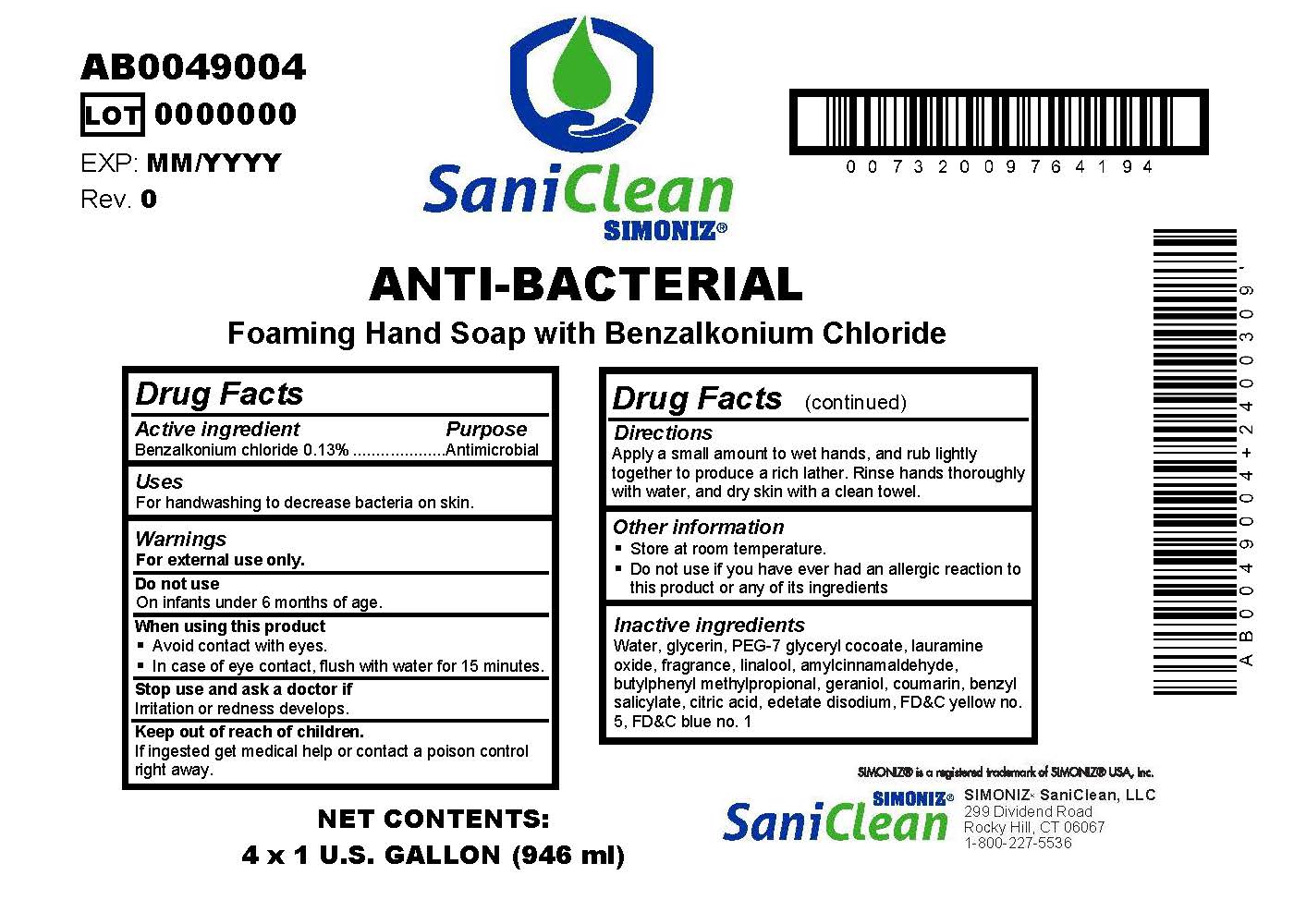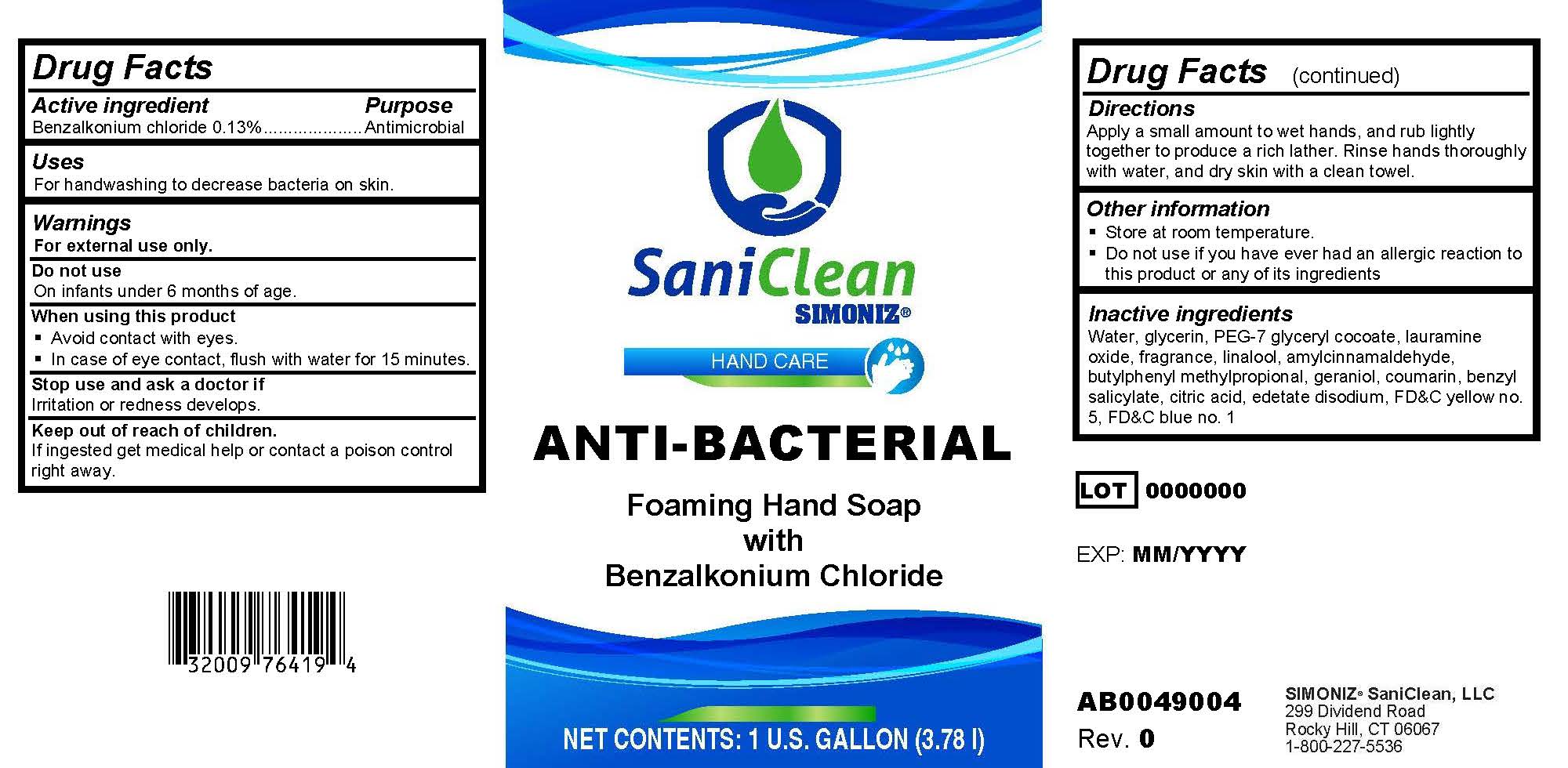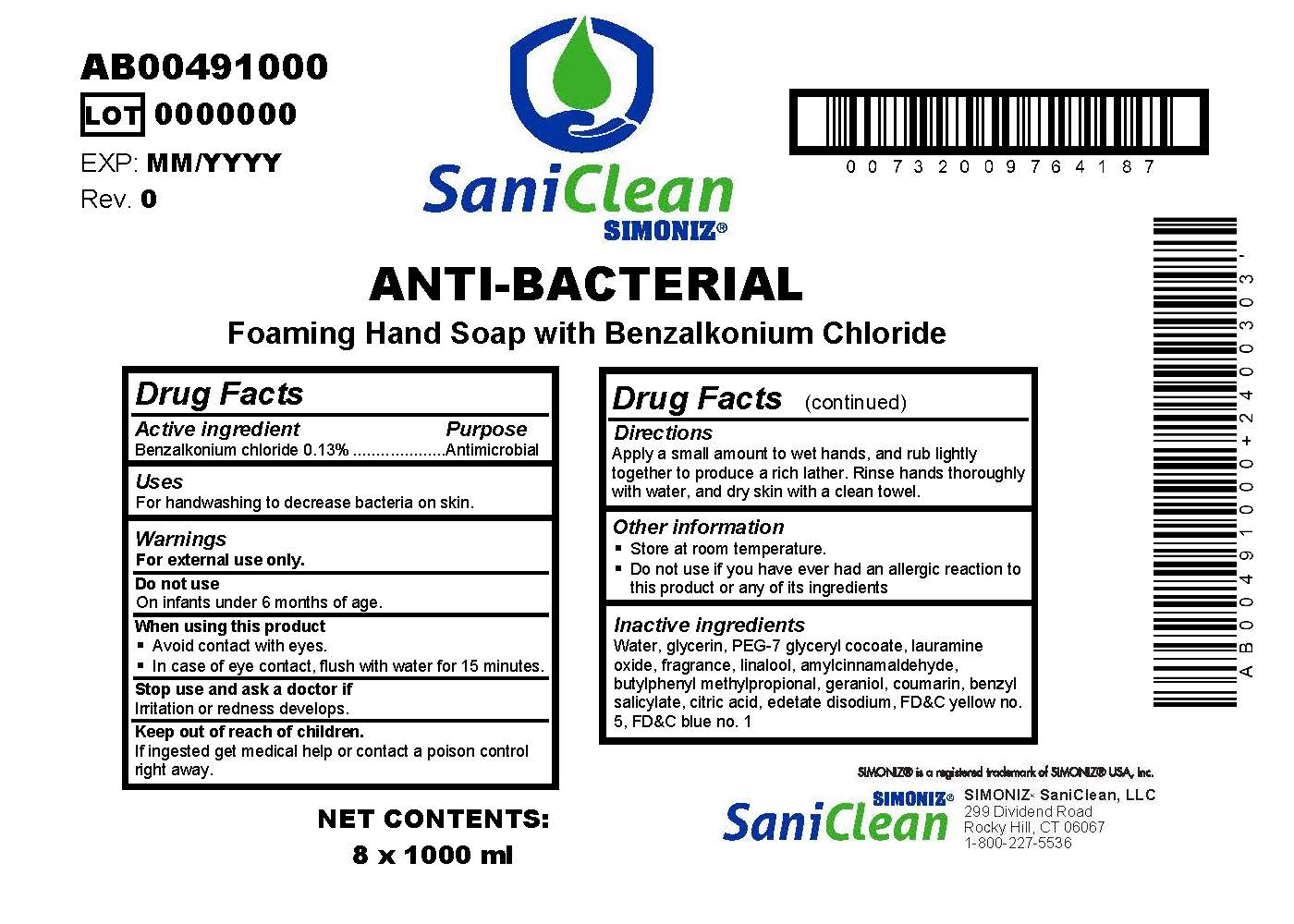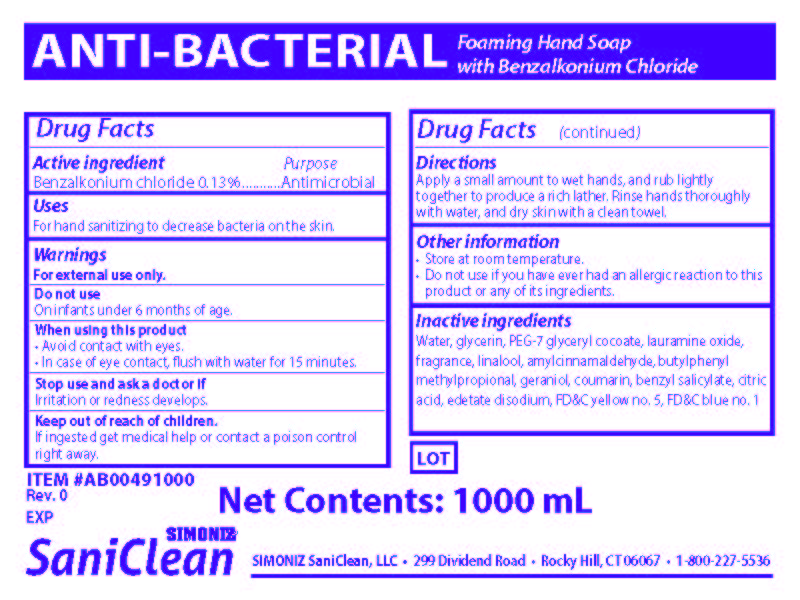 DRUG LABEL: Saniclean
NDC: 63900-110 | Form: SOAP
Manufacturer: Simoniz Saniclean, LLC
Category: otc | Type: HUMAN OTC DRUG LABEL
Date: 20251105

ACTIVE INGREDIENTS: BENZALKONIUM CHLORIDE 0.13 g/100 mL
INACTIVE INGREDIENTS: EDETATE DISODIUM; BENZYL SALICYLATE; COUMARIN; GERANIOL; .ALPHA.-AMYLCINNAMALDEHYDE; FD&C YELLOW NO. 5; WATER; LAURAMINE OXIDE; PEG-7 GLYCERYL COCOATE; ANHYDROUS CITRIC ACID; GLYCERIN; BUTYLPHENYL METHYLPROPIONAL; LINALOOL, (+/-)-; FD&C BLUE NO. 1

Anti-Baterial Foaming Hand Soap with 0.13% Benzalkonium Chloride

Active ingredient

Benzalkonium chloride 0.13%

Purpose

Antimicrobial

Uses

For handwashing to decrease bateria on skin.

Warnings

For external use only.

Do not use

On infants under 5 months of age.

When using this product

- Avoid contact with eyes.
- In case of eye contact, flush with water for 15 minutes.

Stop use and ask a doctor if

Irritation or redness develops.

Keep out of reach of children.

If ingested get medical help or contact a poison control right away.

Directions

Apply a small amount to wet hands, and rub lightly together to produce a rich lather. Rinse hands thoroughly with water, and dry skin with a clean towel.

Other Information

- Store at room temperature.
- Do not use if you have ever had an allergic reaction to this product or any of its ingredients

Inactive ingredients

Water, glycerin, PEG-7 glyceryl cocoate, lauramine oxide, fragrance, linalool, amylcinnamaldehyde, butylphenyl methylpropional, geraniol, coumarin, benzyl salicylate, citric acid, edetate disodium, FD&C yellow no. 5, FD&C blue no. 1

LOT

EXP:

Simoniz Saniclean, LLC

299 Dividend Road

Rocky Hill, CT 06067

1-800-227-5536

1 U.S. Gallon Bottle

ANTI-BACTERIAL

Foaming Hand Soap

with

Benzalkonium Chloride

NET CONTENTS: 1 U.S. Gallon (3.78 l)

1,000 ml bag

Anti-Bacterial

Foaming Hand Soap with Benzalkonium Chloride

Net Contents: 1000 mL

Simoniz Saniclean, LLC

299 Dividend Road

Rocky Hill, CT 06067

1-800-227-5536